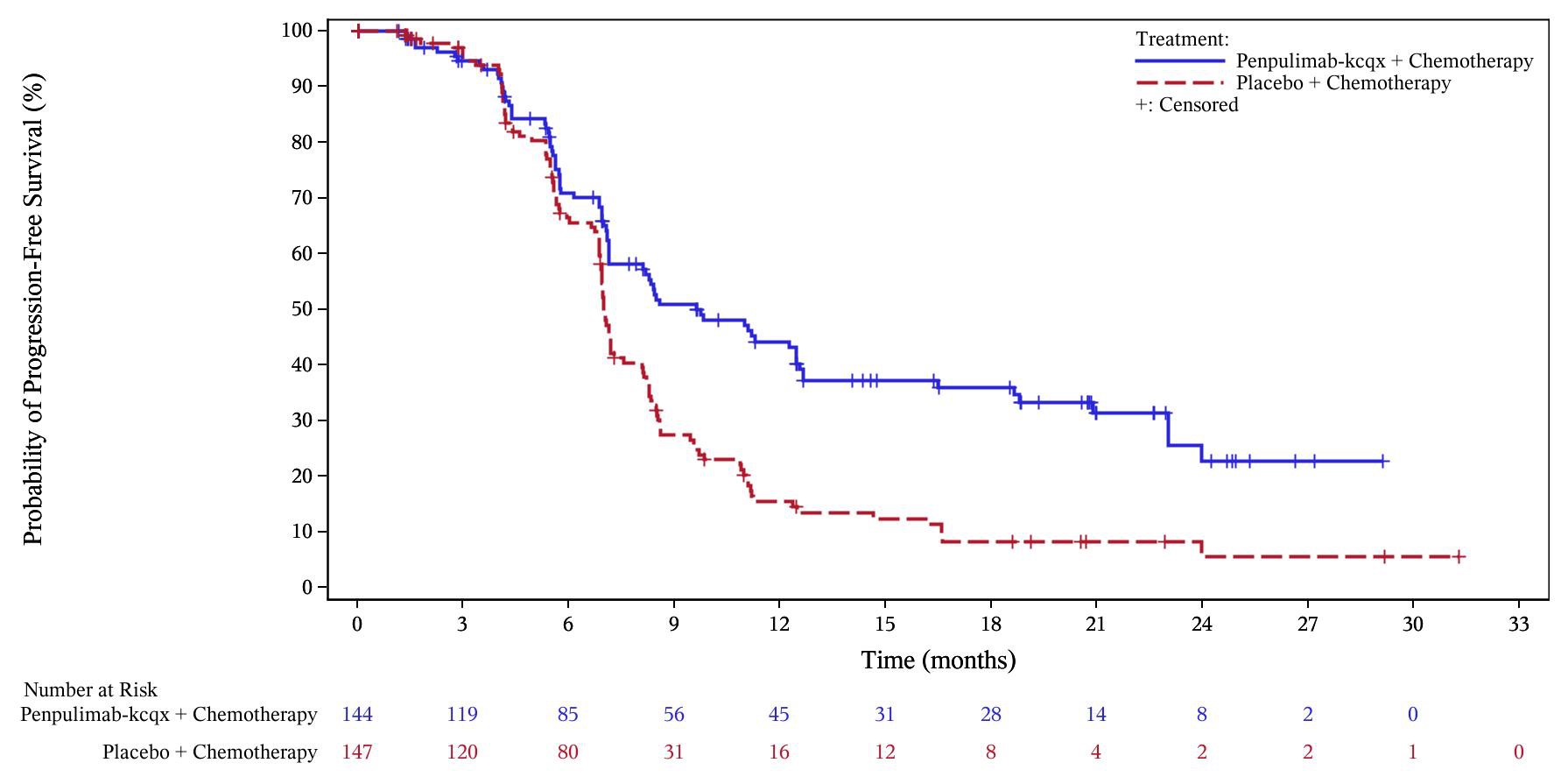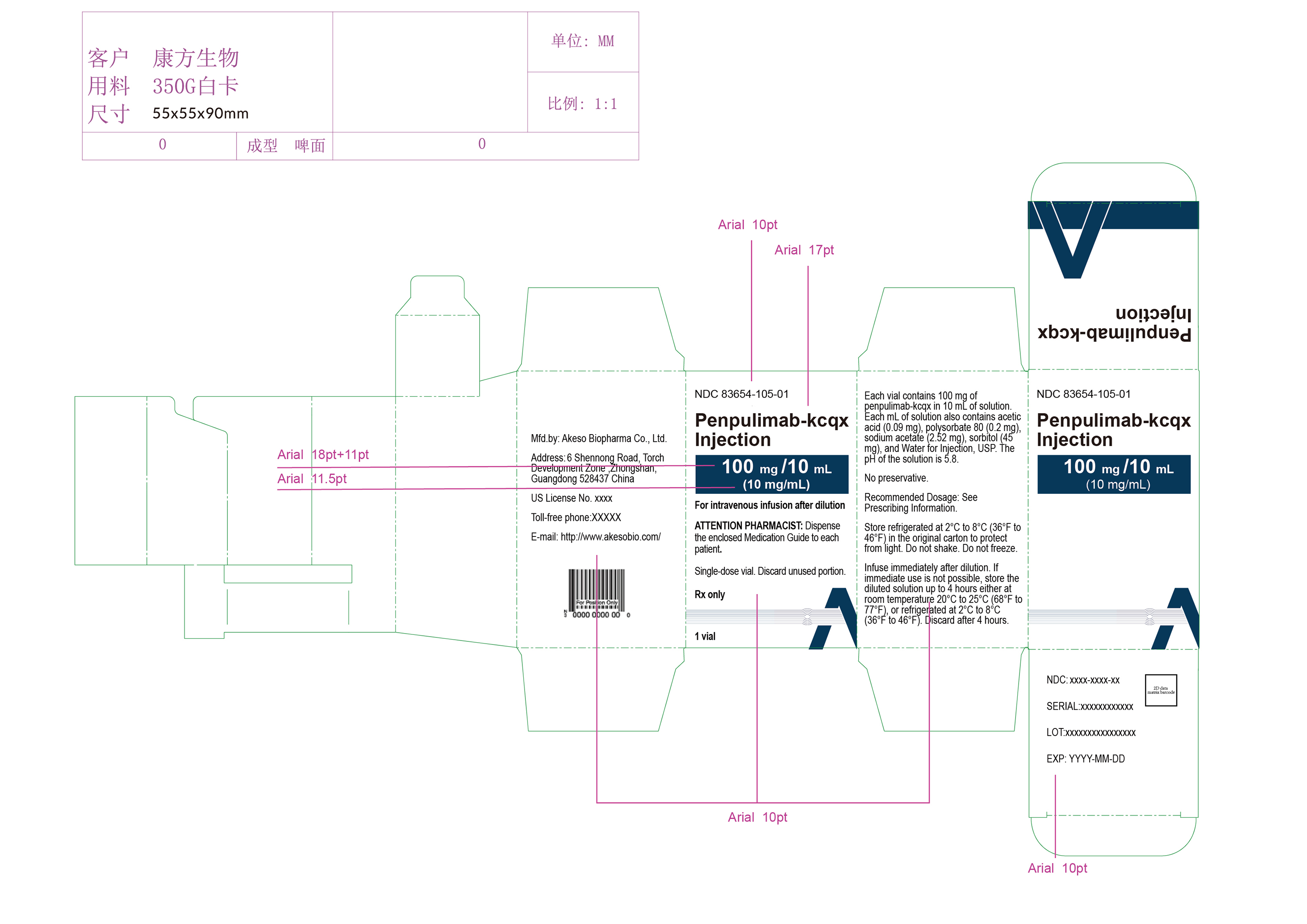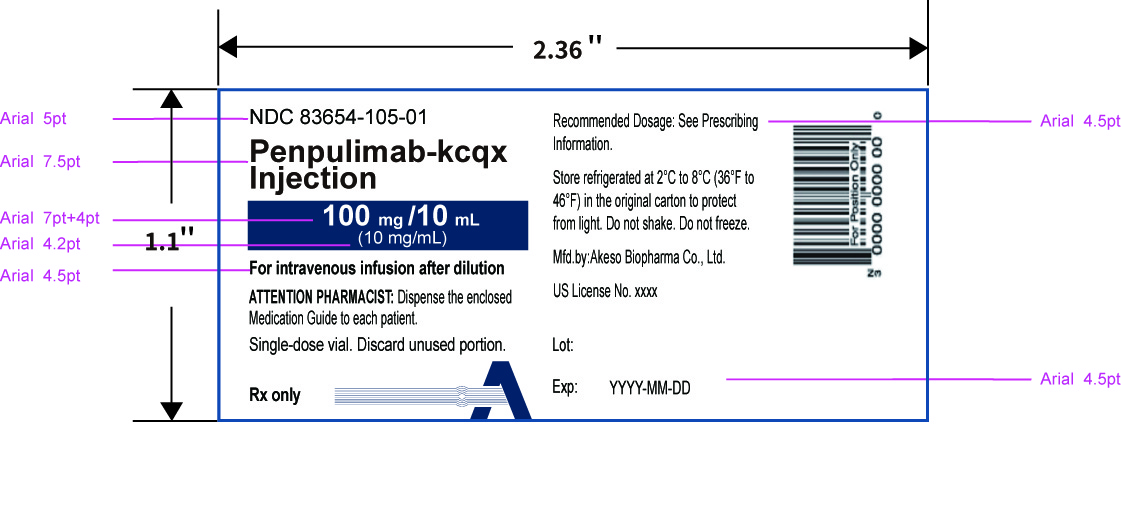 DRUG LABEL: Penpulimab
NDC: 83654-105 | Form: INJECTION
Manufacturer: Akeso Biopharma, Co., Ltd
Category: prescription | Type: HUMAN PRESCRIPTION DRUG LABEL
Date: 20250424

ACTIVE INGREDIENTS: PENPULIMAB 100 mg/10 mL
INACTIVE INGREDIENTS: ACETIC ACID 0.9 mg/10 mL; SORBITOL 450 mg/10 mL; SODIUM ACETATE 25.2 mg/10 mL; POLYSORBATE 80 2 mg/10 mL

HIGHLIGHTS OF PRESCRIBING INFORMATION

These highlights do not include all the information needed to use PENPULIMAB-KCQX safely and effectively. See full prescribing information for PENPULIMAB-KCQX.
PENPULIMAB-KCQX injection, for intravenous use
Initial U.S. Approval: 2025

1 INDICATIONS AND USAGE

Penpulimab-kcqx is a programmed death receptor-1 (PD-1)-blocking antibody indicated:

in combination with either cisplatin or carboplatin and gemcitabine for the first-line treatment of adults with recurrent or metastatic non-keratinizing nasopharyngeal carcinoma (NPC) (1.1)
as a single agent for the treatment of adults with metastatic non-keratinizing NPC with disease progression on or after platinum-based chemotherapy and at least one other prior line of therapy. (1.2)

2 DOSAGE AND ADMINISTRATION

Penpulimab-kcqx in combination with either cisplatin or carboplatin and gemcitabine:

- 200 mg intravenously over 60 minutes every 3 weeks until disease progression or a maximum of 24 months. (2.1)

Penpulimab-kcqx as a single agent:

- 200 mg intravenously over 60 minutes every 2 weeks until disease progression or a maximum of 24 months. (2.2)

Dilute prior to administration. (2.4)

3 DOSAGE FORMS AND STRENGTHS

Injection: 100 mg/10 mL (10 mg/mL) solution in a single-dose vial.(3)

4 CONTRAINDICATIONS

None.(4)

5 WARNINGS AND PRECAUTIONS

- Immune-Mediated Adverse Reactions (5.1)

o Immune-mediated adverse reactions, which may be severe or fatal, can occur in any organ system or tissue, including the following: immune-mediated pneumonitis, immune-mediated colitis, immune-mediated hepatitis and hepatotoxicity, immune-mediated

endocrinopathies, immune-mediated dermatologic adverse reactions, immune-mediated nephritis and renal dysfunction, immune-mediated dermatologic adverse reactions and solid organ transplant rejection.

o Monitor for early identification and management. Evaluate liver enzymes, creatinine, and thyroid function at baseline and periodically during treatment.

o Withhold or permanently discontinue penpulimab-kcqx based on severity and type of reaction.

- Infusion-Related Reactions: Interrupt, slow the rate of infusion, or permanently discontinue penpulimab-kcqx based on the severity of the reaction. (5.2)
- Complications of Allogeneic HSCT: Fatal and other serious complications can occur in patients who receive allogeneic HSCT before or after being treated with a PD-1/PD-L1 blocking antibody. (5.3)
- Embryo-Fetal Toxicity: Can cause fetal harm. Advise females of reproductive potential of the potential risk to a fetus and to use effective contraception. (5.4, 8.1, 8.3)

6 ADVERSE REACTIONS

Penpulimab-kcqx in combination with either cisplatin or carboplatin and gemcitabine: The most common adverse reactions (≥20%) were nausea, vomiting, hypothyroidism, constipation, decreased appetite, decreased weight, cough, COVID-19 infection, fatigue, rash, and pyrexia. (6.1)

Penpulimab-kcqx as a single agent: The most common adverse reactions (≥20%) were anemia and hypothyroidism. (6.1)

To report SUSPECTED ADVERSE REACTIONS, contact Akeso Biopharma Co., Ltd. at toll-free phone 833-662-5376 or FDA at 1-800-FDA-1088 or www.fda.gov/medwatch.

8 USE IN SPECIFIC POPULATIONS

Lactation: Advise not to breastfeed (8.2)

See 17 for PATIENT COUNSELING INFORMATION and Medication Guide.

FULL PRESCRIBING INFORMATION

1 INDICATIONS AND USAGE

1.1 First-line Treatment of Recurrent or Metastatic Non-Keratinizing Nasopharyngeal Carcinoma

Penpulimab-kcqx, in combination with either cisplatin or carboplatin and gemcitabine, is indicated for the first-line treatment of adults with recurrent or metastatic non-keratinizing nasopharyngeal carcinoma (NPC).

1.2 Recurrent Metastatic Non-Keratinizing Nasopharyngeal Carcinoma

Penpulimab-kcqx, as a single agent, is indicated for the treatment of adults with metastatic non-keratinizing NPC and disease progression on or after platinum-based chemotherapy and at least one other prior line of therapy.

2 DOSAGE AND ADMINISTRATION

2.1 Recommended Dosage of Penpulimab-kcqx in Combination with Either Cisplatin or Carboplatin and Gemcitabine – Every 3 Week Dosing

First-line Treatment of Recurrent or Metastatic Nasopharyngeal Carcinoma

The recommended dosage of penpulimab-kcqx is 200 mg administered as an intravenous infusion over 60 minutes every 3 weeks until disease progression or unacceptable toxicity, for a maximum of 24 months.

Table 1 Order of Administration and Regimen for Penpulimab-kcqx in Combination with Either Cisplatin or Carboplatin and Gemcitabine

Administer the regimen in the following order: penpulimab-kcqx first, gemcitabine second and cisplatin or carboplatin last.
Drug and Dose | Duration/ Timing of Treatment
penpulimab-kcqx 200 mg intravenously | Every 3 weeks for 6 cycles, and then every 3 weeks until unacceptable toxicity or disease progression for a maximum of 24 months
gemcitabine 1000 mg/m^2 intravenously | Every 3 weeks for 6 cycles
cisplatin 80 mg/m^2 intravenously; or; carboplatin AUC 5 intravenously | Every 3 weeks for 6 cycles

2.2 Recommended Dosage of Penpulimab-kcqx as a Single Agent – Every 2 Week Dosing

Recurrent Metastatic Non-Keratinizing Nasopharyngeal Carcinoma

The recommended dosage of penpulimab-kcqx is 200 mg administered as an intravenous infusion over 60 minutes every 2 weeks until disease progression or unacceptable toxicity, for a maximum of 24 months.

2.3 Dosage Modifications of Penpulimab-kcqx for Adverse Reactions

No dose reduction for penpulimab-kcqx is recommended. In general, withhold penpulimab-kcqx for severe (Grade 3) immune-mediated adverse reactions. Permanently discontinue penpulimab-kcqx for life-threatening (Grade 4) immune-mediated adverse reactions, recurrent severe (Grade 3) immune-mediated reactions that require systemic immunosuppressive treatment, or an inability to reduce corticosteroid dose to 10 mg or less of prednisone or equivalent per day within 12 weeks of initiating steroids.

Dosage modifications for penpulimab-kcqx in combination or penpulimab-kcqx as a single agent for adverse reactions that require management different from these general guidelines are summarized in Table 2.

Table 2 Recommended Dosage Modification for Adverse Reactions

Adverse Reaction | Severity* | Dosage Modification
Immune-Mediated Adverse Reactions [see Warnings and Precautions (5.1)]
Pneumonitis | Grade 2 | Withhold†
Pneumonitis | Grade 3 or 4 | Permanently discontinue
Colitis | Grade 2 or 3 | Withhold†
Colitis | Grade 4 | Permanently discontinue
Hepatitis with no tumor involvement of the liver | AST or ALT increases to more than 3 and up to 8 times ULN; or; Total bilirubin increases to more than 1.5 and up to 3 times ULN | Withhold†
Hepatitis with no tumor involvement of the liver | AST or ALT increases to more than 8 times ULN; or; Total bilirubin increases to more than 3 times ULN | Permanently discontinue
Hepatitis with tumor involvement of the liver‡ | Baseline AST or ALT is more than 1 and up to 3 times ULN and increases to more than 5 and up to 10 times ULN or; Baseline AST or ALT is more than 3 and up to 5 times ULN and increases to more than 8 and up to 10 times ULN | Withhold†
Hepatitis with tumor involvement of the liver‡ | ALT or AST increases to more than 10 times ULN; or; Total bilirubin increases to more than 3 times ULN | Permanently discontinue
Endocrinopathies | Grade 3 or 4 | Withhold until clinically stable or permanently discontinue depending on severity
Nephritis with Renal Dysfunction | Grade 2 or 3 increased blood creatinine | Withhold†
Nephritis with Renal Dysfunction | Grade 4 increased blood creatinine | Permanently discontinue
Exfoliative Dermatologic Conditions | Suspected SJS, TEN, or DRESS | Withhold†
Exfoliative Dermatologic Conditions | Confirmed SJS, TEN, or DRESS | Permanently discontinue
Myocarditis | Grade 2, 3, or 4 | Permanently discontinue
Neurological Toxicities | Grade 2 | Withhold†
Neurological Toxicities | Grade 3 or 4 | Permanently discontinue
Other Adverse Reactions
Infusion-Related Reactions [see Warnings and Precautions (5.2) ] | Grade 1 or 2 | Interrupt or slow the rate of infusion
Infusion-Related Reactions [see Warnings and Precautions (5.2) ] | Grade 3 or 4 | Permanently discontinue

*Based on Common Terminology Criteria for Adverse Events (CTCAE), version 5.0

†Resume in patients with complete or partial resolution (Grades 0 to 1) after corticosteroid taper. Permanently discontinue if no complete or partial resolution within 12 weeks of initiating steroids or inability to reduce prednisone to 10 mg per day or less (or equivalent) within 12 weeks of initiating steroids.

‡If AST and ALT are less than or equal to ULN at baseline, withhold or permanently discontinue penpulimab-kcqx based on recommendations for hepatitis with no liver involvement.

ALT = alanine aminotransferase, AST = aspartate aminotransferase, DRESS = Drug Rash with Eosinophilia and Systemic Symptoms, SJS = Stevens Johnson Syndrome, TEN = toxic epidermal necrolysis, ULN = upper limit of normal

2.4 Preparation and Administration

Preparation and Storage of Diluted Solution

- Inspect the solution for particulate matter and discoloration. The solution is clear to slightly opalescent, colorless to yellowish. Discard the vial if the solution is cloudy, discolored, or contains visible particles.
- Dilute penpulimab-kcqx injection prior to intravenous administration.
- Withdraw the required volume from two vials of penpulimab-kcqx and transfer into an intravenous (IV) bag containing 100 mL or less of 0.9% Sodium Chloride Injection, USP.
- Gently invert the bag to mix the diluted solution .Do not shake.
- The final concentration of the diluted solution should be between 2 mg/mL to 5 mg/mL.
- Discard any unused portion left in the vial.
- The product does not contain a preservative.
- Administer diluted solution immediately once prepared. If diluted solution is not administered immediately the total time from dilution to the end of the infusion should not exceed 4 hours. Store the diluted solution up to 4 hours either at room temperature 20°C to 25°C (68°F to 77°F), or refrigerated at 2°C to 8°C (36°F to 46°F). Discard after 4 hours.
- Do not freeze.

Administration

- Administer diluted solution intravenously over 60 minutes through an intravenous line containing a sterile, non-pyrogenic, low-protein binding 0.2 micron to 0.22 micron in-line or add-on filter.
- Do not co-administer other drugs through the same infusion line.

3 DOSAGE FORMS AND STRENGTHS

Injection: 100 mg/10 mL (10 mg/mL) as a clear to slightly opalescent, colorless to yellowish solution in a single-dose vial.

4 CONTRAINDICATIONS

None.

5 WARNINGS AND PRECAUTIONS

5.1 Severe and Fatal Immune-Mediated Adverse Reactions

Penpulimab-kcqx is a monoclonal antibody that belongs to a class of drugs that bind to either the programmed death-receptor 1 (PD-1) or the PD-ligand 1 (PD-L1), blocking the PD-1/PD-L1 pathway, thereby removing inhibition of the immune response, potentially breaking peripheral tolerance and inducing immune-mediated adverse reactions. Important immune-mediated adverse reactions listed under WARNINGS AND PRECAUTIONS may not include all possible severe and fatal immune-mediated reactions.

Immune-mediated adverse reactions, which may be severe or fatal, can occur in any organ system or tissue and can affect more than one body system simultaneously. Immune-mediated adverse reactions can occur at any time after starting treatment with a PD-1/PD- L1 blocking antibody. While immune-mediated adverse reactions usually manifest during treatment with PD-1/PD-L1 blocking antibodies, immune-mediated adverse reactions can also manifest after discontinuation of PD-1/PD-L1 blocking antibodies.

Early identification and management of immune-mediated adverse reactions are essential to ensure safe use of PD-1/PD-L1 blocking antibodies. Monitor patients closely for symptoms and signs that may be clinical manifestations of underlying immune-mediated adverse reactions. Evaluate liver enzymes, creatinine, and thyroid function at baseline and periodically during treatment. In cases of suspected immune-mediated adverse reactions, initiate appropriate workup to exclude alternative etiologies, including infection. Institute medical management promptly, including specialty consultation as appropriate.

Withhold or permanently discontinue penpulimab-kcqx depending on severity [see Dosage and Administration (2) ].In general, if penpulimab-kcqx requires interruption or discontinuation, administer systemic corticosteroid therapy (1 mg to 2 mg/kg/day prednisone or equivalent) until improvement to Grade 1 or less. Upon improvement to Grade 1 or less, initiate corticosteroid taper and continue to taper over at least 1 month [ see Dosage and A dministration (2)]. Consider administration of other systemic immunosuppressants in patients whose immune-mediated adverse reactions are not controlled with corticosteroid therapy.

Toxicity management guidelines for adverse reactions that do not necessarily require systemic steroids (e.g., endocrinopathies and dermatologic reactions) are discussed below.

Immune-Mediated Pneumonitis

Penpulimab-kcqx can cause immune-mediated pneumonitis. In patients treated with other PD-1/PD-L1 blocking antibodies, the incidence of pneumonitis is higher in patients who have received prior thoracic radiation.

Penpulimab-kcqx in Combinationwith Either Cisplatin or Carboplatin and Gemcitabine

Immune-mediated pneumonitis occurred in 0.7% (1/146) of patients receiving penpulimab-kcqx, which was a Grade 2 (0.7%) adverse reaction. Systemic corticosteroids were required in the patient. Pneumonitis led to withholding of penpulimab-kcqx in the patient.

Penpulimab-kcqx as a Single Agent

Immune-mediated pneumonitis occurred in 1.3% (5/372) of patients receiving penpulimab-kcqx, including Grade 3 (0.5%), Grade 2 (0.5%) and Grade 1 (0.3%) adverse reactions. Systemic corticosteroids were required in 80% (4/5) of patients with pneumonitis. Pneumonitis led to permanent discontinuation of penpulimab-kcqx in 0.8% (3/372). Pneumonitis resolved in 20% (1/5) of these patients.

Immune-Mediated Colitis

Penpulimab-kcqx can cause immune-mediated colitis, which may present with diarrhea. Cytomegalovirus (CMV) infection/reactivation can occur in patients with corticosteroid-refractory immune-mediated colitis. In cases of corticosteroid-refractory colitis, consider repeating infectious workup to exclude alternative etiologies.

Penpulimab-kcqx as a Single Agent

Immune-mediated colitis occurred in 1.1% (4/372) of patients receiving penpulimab-kcqx, including Grade 2 (0.8%) and Grade 1 (0.3%) adverse reactions. Systemic corticosteroids were required in 75% (3/4) of patients with colitis. Colitis led to withholding of penpulimab-kcqx in 0.8% (3/372) of patients.

Immune-Mediated Hepatitis and Hepatotoxicity

Penpulimab-kcqx can cause immune-mediated hepatitis.

Penpulimab-kcqx in Combinationwith Either Cisplatin or Carboplatin and Gemcitabine

Immune-mediated hepatitis occurred in 0.7% (1/146) of patients receiving penpulimab-kcqx in combination with either cisplatin or carboplatin and gemcitabine, which was a Grade 2 (0.7%) adverse reaction. Systemic corticosteroids and withholding of penpulimab-kcqx were required in this patient.

Penpulimab-kcqx as a Single Agent

Immune-mediated hepatitis occurred in 3.8% (14/372) of patients receiving penpulimab-kcqx, including Grade 3 (0.8%), Grade 2 (1.3%) and Grade 1 (1.6%) adverse reactions. Systemic corticosteroids were required in 14% (2/14) of patients with hepatitis. Hepatitis led to permanent discontinuation of penpulimab-kcqx in 0.3% (1/372) and withholding of penpulimab-kcqx in 2.2% (8/372) of patients. Hepatitis resolved in 64% (9/14) of these patients.

Immune-Mediated Endocrinopathies

Adrenal Insufficiency

Penpulimab-kcqx can cause primary or secondary adrenal insufficiency. For Grade 2 or higher adrenal insufficiency, initiate symptomatic treatment, including hormone replacement as clinically indicated. Withhold penpulimab-kcqx depending on severity [see Dosage and Administration (2.2)].

Hypophysitis

Penpulimab-kcqx can cause immune-mediated hypophysitis. Hypophysitis can present with acute symptoms associated with mass effect such as headache, photophobia, or visual field defects. Hypophysitis can cause hypopituitarism. Initiate hormone replacement as indicated. Withhold or permanently discontinue penpulimab-kcqx depending on severity [see Dosage and Administration (2.2)].

Thyroid Disorders:

Penpulimab-kcqx can cause immune-mediated thyroid disorders. Thyroiditis can present with or without endocrinopathy. Hypothyroidism can follow hyperthyroidism. Initiate hormone replacement therapy for hypothyroidism or institute medical management of hyperthyroidism as clinically indicated. Withhold or permanently discontinue penpulimab-kcqx based on the severity [see Dosage and Administration (2) ] .

Penpulimab-kcqx in Combinationwith Either Cisplatin or Carboplatin and Gemcitabine

Hyperthyroidism: Immune-mediated hyperthyroidism occurred in 2.1% (3/146) of patients receiving penpulimab-kcqx in combination with either cisplatin or carboplatin and gemcitabine, including Grade 2 (0.7%) and Grade 1 (1.4%) adverse reactions.

Hypothyroidism: Immune-mediated hypothyroidism occurred in 16% (26/146) of patients receiving penpulimab-kcqx in combination with either cisplatin or carboplatin and gemcitabine, including Grade 2 (13%) and Grade 1 (4.8%) adverse reactions. Penpulimab-kcqx was withheld in 0.7% (1/146) of patients. Hypothyroidism resolved in 12% (3/26) of these patients.

Penpulimab-kcqx as a Single Agent

Thyroiditis: Thyroiditis occurred in 0.5% (2/372) of patients receiving penpulimab-kcqx, including Grade 2 (0.3%) and Grade 1 (0.3%) adverse reactions. Thyroiditis led to withholding of penpulimab-kcqx in 0.3% (1/372) of patients. Thyroiditis was resolved in 50% (1/2) of patients.

Hyperthyroidism:Immune-mediated hyperthyroidism occurred in 7% (24/372) of patients receiving penpulimab-kcqx, including Grade 2 (1.1%) and Grade 1 (5%) adverse reactions. Penpulimab-kcqx was withheld in 0.5% (2/372) of patients. Hyperthyroidism resolved in 79% (19/24) of these patients.

Hypothyroidism: Immune-mediated hypothyroidism occurred in 19% (69/372) of patients receiving penpulimab-kcqx, including Grade 2 (7%) and Grade 1 (12%) adverse reactions. Penpulimab-kcqx was withheld in 1.6% (6/372) of patients. Hypothyroidism resolved in 48% (33/69) of these patients.

Type 1 Diabetes Mellitus, which can present with Diabetic Ketoacidosis

Monitor patients for hyperglycemia or other signs and symptoms of diabetes. Initiate treatment with insulin as clinically indicated. Withhold penpulimab-kcqx depending on severity [see Dosage and Administration (2) ].

Penpulimab-kcqx in Combinationwith Either Cisplatin or Carboplatin and Gemcitabine

Diabetes occurred in 2.7% (4/146) of patients receiving penpulimab-kcqx in combination with either cisplatin or carboplatin and gemcitabine, including Grade 4 (0.7%), Grade 3 (0.7%), Grade 2 (0.7%) and Grade 1 (0.7%) adverse reactions. Diabetes led to permanent discontinuation of penpulimab-kcqx in 0.7% (1/146) and withholding of penpulimab-kcqx in 0.7% (1/146) of patients. Diabetes was resolving in 75% (3/4) of these patients.

Penpulimab-kcqx as a Single Agent

Diabetes occurred in 0.8% (3/372) of patients receiving penpulimab-kcqx as a single agent, including Grade 1 (0.8%) adverse reactions. Diabetes resolved in 67% (2/3) of these patients.

Immune-Mediated Nephritis with Renal Dysfunction

Penpulimab-kcqx can cause immune-mediated nephritis and renal dysfunction.

Penpulimab-kcqx as a Single Agent

Immune-mediated nephritis occurred in 0.5% (2/372) of patients receiving penpulimab-kcqx, including Grade 3 (0.3%) and Grade 2 (0.3%) adverse reactions. Immune-mediated nephritis led to permanent discontinuation of penpulimab-kcqx in 0.5% (2/372) of patients. Systemic corticosteroids were required in 50% (1/2) of patients. Nephritis resolved in 50% (1/2) of these patients.

Immune-Mediated Dermatologic Adverse Reactions

Penpulimab-kcqx can cause immune-mediated rash or dermatitis. Exfoliative dermatitis, including Stevens Johnson Syndrome (SJS), Drug Rash with Eosinophilia and Systemic Symptoms (DRESS), and Toxic Epidermal Necrolysis (TEN) has occurred with PD-1/L-1 blocking antibodies. Topical emollients and/or topical corticosteroids may be adequate to treat mild to moderate non-exfoliative rashes. Withhold or permanently discontinue penpulimab-kcqx depending on severity [see Dosage and Administration (2)].

Penpulimab-kcqx in Combinationwith Either Cisplatin or Carboplatin and Gemcitabine

Immune-mediated rash or dermatitis occurred in 10% (14/146) of patients receiving penpulimab-kcqx in combination with either cisplatin or carboplatin and gemcitabine, including Grade 3 (0.7%), Grade 2 (4.8%) and Grade 1 (4.1%) adverse reactions. Systemic corticosteroids were required in 36% (5/14) of patients with immune-mediated rash or dermatitis. Immune-mediated rash or dermatitis led to withholding of penpulimab-kcqx in 1.4% (2/146) of patients. Immune-mediated rash or dermatitis resolved in 78.6% (11/14) of these patients.

Penpulimab-kcqx as a Single Agent

Immune-mediated rash or dermatitis occurred in 12% (43/372) of patients receiving penpulimab-kcqx, including Grade 3 (1.3%), Grade 2 (3.5%) and Grade 1 (7%) adverse reactions. Systemic corticosteroids were required in 14% (6/43) of patients with immune-mediated rash or dermatitis. Immune-mediated rash or dermatitis led to permanent discontinuation of penpulimab-kcqx in 0.3% (1/372) and withholding of penpulimab-kcqx in 1.6% (6/372) of patients. Immune-mediated rash or dermatitis resolved in 58% (25/43) of these patients.

Other Immune-Mediated Adverse Reactions

The following clinically significant immune-mediated adverse reactions occurred at an incidence of <1% (unless otherwise noted) in patients who received penpulimab-kcqx in combination with either cisplatin or carboplatin and gemcitabine or single-agent penpulimab-kcqx or were reported with the use of other PD-1/PD-L1 blocking antibodies. Severe or fatal cases have been reported for some of these adverse reactions.

Cardiac/vascular: Myocarditis, pericarditis, vasculitis.

Nervous system: Meningitis, encephalitis, myelitis and demyelination, myasthenic syndrome/myasthenia gravis (including exacerbation), Guillain-Barré syndrome, nerve paresis, autoimmune neuropathy, nerve injury.

Ocular:Uveitis, iritis, and other ocular inflammatory toxicities can occur. Some cases can be associated with retinal detachment. Various grades of visual impairment including blindness can occur. If uveitis occurs in combination with other immune-mediated adverse reactions, consider a Vogt-Koyanagi-Harada-like syndrome, as this may require treatment with systemic steroids to reduce the risk of permanent vision loss.

Gastrointestinal:Pancreatitis to include increases in serum amylase and lipase levels, gastritis, duodenitis.

Musculoskeletal and Connective Tissue:Myositis/polymyositis, rhabdomyolysis and associated sequelae including renal failure, arthritis, polymyalgia rheumatic.

Endocrine: Hypoparathyroidism.

Hematologic/Immune: Hemolytic anemia, aplastic anemia, hemophagocytic lymphohistiocytosis, systemic inflammatory response syndrome, histiocytic necrotizing lymphadenitis (Kikuchi lymphadenitis), sarcoidosis, immune thrombocytopenic purpura, solid organ transplant rejection, other transplant (including corneal graft) rejection.

5.2 Infusion-Related Reactions

Penpulimab-kcqx can cause severe or life-threatening infusion-related reactions, including hypersensitivity and anaphylaxis. Discontinue penpulimab-kcqx in patients with severe or life-threatening infusion-related reactions. Interrupt or slow the rate of infusion in patients with mild or moderate infusion-related reactions [see Dosage and Administration (2) ].

Penpulimab-kcqx in Combinationwith Either Cisplatin or Carboplatin and Gemcitabine

Infusion-related reactions occurred in 3.4% of 146 patients receiving penpulimab-kcqx in combination with either cisplatin or carboplatin and gemcitabine, including Grade 2 (1.4%) and Grade 1 (2.1%) infusion related reactions.

Penpulimab-kcqx as a Single Agent

Infusion-related reactions occurred in 10% of 372 patients receiving penpulimab-kcqx as single agent, including Grade 4 (0.3%), Grade 3 (0.3%), Grade 2 (6%) and Grade 1 (3.8%) infusion related reactions. Penpulimab-kcqx was withheld in 0.8% (3/372) and permanently discontinued in 0.3% (1/372) of patients.

5.3 Complications of Allogeneic HSCT

Fatal and other serious complications can occur in patients who receive allogeneic hematopoietic stem cell transplantation (HSCT) before or after being treated with a PD-1/PD-L1 blocking antibody. Transplant-related complications include hyperacute graft-versus-host-disease (GVHD), acute GVHD, chronic GVHD, hepatic veno-occlusive disease (VOD) after reduced intensity conditioning, and steroid-requiring febrile syndrome (without an identified infectious cause) [see Adverse Reactions (6.1)].These complications may occur despite intervening therapy between PD-1/PD-L1 blockade and Allogeneic HSCT.

Follow patients closely for evidence of transplant-related complications and intervene promptly. Consider the benefit versus risks of treatment with a PD-1/PD-L1 blocking antibody prior to or after an Allogeneic HSCT.

5.4 Embryo-Fetal Toxicity

Based on its mechanism of action, penpulimab-kcqx can cause fetal harm when administered to a pregnant woman. Animal studies have demonstrated that inhibition of the PD-1/PD-L1 pathway can lead to increased risk of immune-mediated rejection of the developing fetus resulting in fetal death. Advise pregnant women of the potential risk to a fetus.

Advise females of reproductive potential to use effective contraception during treatment with penpulimab-kcqx and for 4 months after the last dose [see Use in Specific Populations (8.1 , 8.3)].

6 ADVERSE REACTIONS

The following adverse reactions are described in other sections of the labeling:

- Severe and Fatal Immune-Mediated Adverse Reactions [see Warnings and Precautions (5.1) ]
- Infusion-Related Reactions[see Warnings and Precautions (5.2) ]
- Complications of Allogeneic HSCT [see Warnings and Precautions (5.3)]

6.1 Clinical Trials Experience

Because clinical trials are conducted under varying conditions, adverse reaction rates observed in the clinical trials of a drug cannot be directly compared to those observed in the clinical trials of another drug and may not reflect the rates observed in practice.

The data described in the WARNINGS AND PRECAUTIONS reflect exposure to penpulimab-kcqx in 146 patients in Study AK105-304 [see Clinical Studies (14.1) ]. Patients received 6 cycles every 3 weeks of intravenous penpulimab-kcqx 200 mg in combination with either cisplatin 80 mg/m^2 or carboplatin AUC 5 and gemcitabine 1000 mg/m^2 followed by single-agent penpulimab-kcqx 200 mg every 3 weeks until disease progression or a maximum of 24 months. Among the 146 patients who received penpulimab-kcqx in combination with either cisplatin or carboplatin and gemcitabine, 71% were exposed for 6 months or longer and 38% were exposed for greater than one year. In this safety population, the most common (≥ 20%) adverse reactions were nausea (58%), vomiting (55%), hypothyroidism (45%), constipation (41%), decreased appetite (36%), decreased weight (26%), cough (25%), COVID-19 infection (25%), fatigue (25%), rash (24%) and pyrexia (21%). The most common Grade 3 to 4 laboratory abnormalities (≥ 2%) were decreased lymphocytes (70%), decreased neutrophils (61%), decreased white blood cells (58%), decreased hemoglobin (49%), decreased platelets (33%), decreased potassium (14%), increased lipase (11%), increased ALT (8%), decreased sodium (7%), increased AST (6%), increased triglycerides (4.3%), decreased magnesium (4.2%), decreased CPK (4.1%), increased amylase (2.9%), increased potassium (2.8%), increased cholesterol (2.2%), increased calcium (2.1%) and increased blood bilirubin (2.1%).

The data described in the WARNINGS AND PRECAUTIONS also reflect exposure to single-agent intravenous penpulimab-kcqx 200 mg every 2 weeks until disease progression or a maximum of 24 months in 372 patients in studies: AK105-101 [NCT03352531], AK-105-201 [NCT03722147], AK105-202 [see Clinical Studies (14.2)], AK105-204 [NCT 04172506]. Among the 372 patients who received single-agent penpulimab-kcqx, 49% were exposed for 6 months or longer and 34% were exposed for at least one year. In this safety population, the most common (≥20%) adverse reactions were anemia (25%) and hypothyroidism (23%). The most common Grade 3 to 4 laboratory abnormalities (≥ 2%) were decreased lymphocytes (11%), increased GGT (9%), decreased phosphate (6%), decreased sodium (4.7%), increased aspartate aminotransferase (4.4%), increased alkaline phosphatase (4%), decreased hemoglobin (3.6%), increased bilirubin (2.7%), increased glucose (3%), increased triglycerides (2.8%), increased alanine aminotransferase (2.5%), increased magnesium (3.3%), and decreased platelets (2.5%).

First line Recurrent or Metastatic Nasopharyngeal Carcinoma

Study AK105-304

The safety of penpulimab-kcqx in combination with either cisplatin or carboplatin and gemcitabine was evaluated in Study AK105-304 [see Clinical Studies (14.1)]. Patients received intravenous placebo or penpulimab-kcqx 200 mg every 3 weeks in combination with 6 cycles of either cisplatin 80 mg/m^2or carboplatin AUC 5 and gemcitabine 1000 mg/m^2every 3 weeks followed by placebo or penpulimab-kcqx 200 mg intravenously every 3 weeks until unacceptable toxicity, disease progression or a maximum of 24 months. Among patients who received penpulimab-kcqx, 71% were exposed for 6 months or longer and 38% were exposed for greater than one year.

The median age of patients who received penpulimab-kcqx was 51 years (23 to 75 years); 82% were male; 97% were Asian, 3.4% were White; 2.1% were Hispanic or Latino, baseline Eastern Cooperative Oncology Group (ECOG) performance score was 0 (36%) or 1 (64%). Of the 146 patients, 69% of patients had received at least one prior systemic therapy and 100% of patients had received prior radiation therapy.

Serious adverse reactions occurred in 51% of patients. The most frequent serious adverse reactions (≥2%) were thrombocytopenia (19%), decreased neutrophils (14%), decreased white blood cells (12%), anemia (8%), myelosuppression (3.4%), decreased sodium (2.7%), pneumonia (2.1%), and nausea (2.1%). Of the patients who received penpulimab-kcqx in combination with either cisplatin or carboplatin and gemcitabine, there was one fatal adverse reaction (0.7%) due to syndrome of inappropriate antidiuretic hormone secretion (SIADH).

Permanent discontinuation of penpulimab-kcqx due to an adverse reaction occurred in 3.4% of patients. Adverse reactions which resulted in permanent discontinuation of penpulimab-kcqx were acute myocardial infarction, acute kidney injury, brain edema, diabetic ketoacidosis, increased potassium, increased lipase, and thrombocytopenia (0.7% each).

Dose interruptions of penpulimab-kcqx due to an adverse reaction occurred in 64% of patients. Adverse reactions which required dose interruption in ≥ 2% of patients included COVID-19 (16%), anemia (16%), thrombocytopenia (14%), decreased white blood cells (14%), decreased neutrophils (10%), pneumonia (10%), increased alanine aminotransferase (3.4%), increased aspartate aminotransferase (2.7%), decreased sodium (2.7%), increased blood creatinine (2.7%), pyrexia (2.1%), and upper respiratory tract infection (2.1%).

Table 3 summarizes the adverse reactions in Study AK105-304.

Table 3 Adverse Reactions (≥ 10%) in Patients with Recurrent or Metastatic NPC Who Received Penpulimab-kcqx in Combination with Either Cisplatin or Carboplatin and Gemcitabine in Study AK105-304

Adverse Reaction | Penpulimab-kcqx Cisplatin or Carboplatin and Gemcitabine N = 146 |  | Placebo Cisplatin or Carboplatin and Gemcitabine N = 142
Adverse Reaction | All Grades^1 (%) | Grade 3 or 4^1 (%) | All Grades^1 (%) | Grade 3 or 4^1 (%)
Gastrointestinal disorders
Nausea | 58 | 2.1 | 64 | 0
Vomiting^2 | 55 | 1.4 | 54 | 1.4
Constipation | 41 | 0 | 44 | 0
Abdominal distension | 12 | 0 | 6 | 0
Endocrine disorders
Hypothyroidism^3 | 45 | 0 | 27 | 0
Metabolism and nutrition disorders
Decreased appetite | 36 | 0 | 39 | 0
Investigations
Weight decreased | 26 | 1.4 | 16 | 0
Respiratory, thoracic and mediastinal disorders
Cough^4 | 25 | 0 | 16 | 0
Infections and infestations
COVID-19 | 25 | 0 | 17 | 0.7
General disorders and administration site conditions
Fatigue^5 | 25 | 1.4 | 22 | 0
Pyrexia | 21 | 0 | 20 | 0.7
Malaise | 10 | 0 | 8 | 0
Skin and subcutaneous tissue disorders
Rash^6 | 24 | 1.4 | 20 | 0
Pruritus | 11 | 0 | 11 | 0
Nervous system disorders
Headache | 15 | 0.7 | 10 | 0.7
Dizziness^7 | 14 | 0 | 15 | 0.7
Renal and urinary disorders
Proteinuria | 14 | 0 | 13 | 0
Acute kidney injury^8 | 13 | 1.4 | 4.9 | 0
Musculoskeletal and connective tissue disorders
Musculoskeletal pain^9 | 14 | 0.7 | 24 | 0
Psychiatric disorders
Insomnia | 12 | 0 | 10 | 0

^1Graded per NCI CTCAE v5.0

^2Includes retching

^3Includes blood thyroid stimulating hormone increased, secondary hypothyroidism

^4Includes productive cough, upper-airway cough syndrome

^5Includes asthenia

^6Includes dermatitis, dermatitis acneiform, drug eruption, eczema, rash maculo-papular, rash papular, rash pustular

^7Includes vertigo

^8Includes acute kidney injury, creatinine renal clearance decreased, glomerular filtration rate decreased, renal failure, renal impairment

^9Includes arthralgia, arthritis, back pain, bone pain, musculoskeletal chest pain, musculoskeletal discomfort, myalgia, neck pain, pain in extremity, spinal pain

Table 4 summarizes the laboratory abnormalities in AK105-304.

Table 4 Select Laboratory Abnormalities (≥20%) That Worsened from Baseline in Patients with Recurrent or Metastatic NPC Who Received Penpulimab-kcqx in Combination with Either Cisplatin or Carboplatin and Gemcitabine in Study AK105-304

Laboratory Abnormality | Penpulimab-kcqx Cisplatin or Carboplatin /Gemcitabine^2 |  | Placebo Cisplatin or Carboplatin /Gemcitabine^3
 | All Grades^1 (%) | Grade 3 or 4^1 (%) | All Grades^1 (%) | Grade 3 or 4^1 (%)
Hematology
White blood cell decreased | 99 | 58 | 97 | 58
Hemoglobin decreased | 98 | 49 | 97 | 47
Lymphocytes decreased | 93 | 70 | 89 | 58
Neutrophils decreased | 92 | 61 | 95 | 65
Chemistry
Magnesium decreased | 69 | 4.2 | 58 | 3.6
Sodium decreased | 62 | 7 | 58 | 7
Triglycerides increased | 58 | 4.3 | 53 | 4.3
Aspartate aminotransferase increased | 52 | 6 | 37 | 2.9
Cholesterol increased | 49 | 2.2 | 46 | 0.7
Creatinine increased | 48 | 1.4 | 39 | 0.7
Albumin decreased | 47 | 0 | 44 | 1.4
Potassium decreased | 45 | 14 | 31 | 3.6
Alanine aminotransferase increased | 42 | 8 | 37 | 2.1
GGT increased | 36 | 1.4 | 33 | 0.7
Alkaline phosphatase increased | 32 | 0.7 | 30 | 0
Lipase increased | 28 | 11 | 23 | 3.9
Chloride decreased | 25 | 1.4 | 11 | 0
Serum amylase increased | 23 | 2.9 | 17 | 0.7
Glucose decreased | 22 | 1.4 | 20 | 0.7
Lipids increased | 21 | 1.4 | 20 | 0.7

^1Toxicity graded according to NCI CTCAE v5.0.

^2The denominator used to calculate the rate varied from 102 to 146 based on the number of patients with a baseline value and at least one post-treatment value.

^3The denominator used to calculate the rate varied from 103 to 142 based on the number of patients with a baseline value and at least one post-treatment value.

Recurrent Metastatic Non-Keratinizing Nasopharyngeal Carcinoma

Study AK105-202

The safety of penpulimab-kcqx as a single agent was evaluated in Study AK105-202 [see Clinical Studies (14.2)].Eligible patients had metastatic non-keratinizing NPC and had received prior platinum-based chemotherapy and at least one other line of therapy or had disease progression within 6 months of completion of platinum-based chemotherapy administered as neoadjuvant, adjuvant, or definitive chemoradiation treatment. Patients received penpulimab-kcqx 200 mg intravenously every 2 weeks until unacceptable toxicity, disease progression, or a maximum of 24 months. Among patients who received penpulimab-kcqx, 45% were exposed for 6 months or longer and 30% for exposed for greater than one year.

The median age of patients who received penpulimab-kcqx was 50 years (20 to 66 years); 76% were male; 100% were Asian, 100% had recurrent disease; baseline Eastern Cooperative Oncology Group (ECOG) performance score was 0 (31%) or 1 (69%). All patients had received at least one prior systemic therapy and prior radiation.

Serious adverse reactions occurred in 22% of patients. Serious adverse reactions in ≥1% were pneumonia (3.8%), pneumonitis (1.5%), respiratory failure (1.5%), rash (1.5%). Fatal adverse reactions occurred in 1% of patients treated with penpulimab-kcqx, including a case each of pneumonitis, septic shock, colitis, and hepatitis.

Permanent discontinuation of penpulimab-kcqx due to an adverse reaction occurred in 3.8% of patients. Adverse reactions which resulted in permanent discontinuation of penpulimab-kcqx in ≥1% were rash, hepatitis, herpes zoster, spinal cord compression and pleural effusion (0.8% each).

Dose interruptions of penpulimab-kcqx due to an adverse reaction occurred in 25% of patients. Adverse reactions which required dose interruption in ≥ 1% of patients included hepatitis (6.2%), anemia (3.1%), pneumonia (3.1%), hypothyroidism (3.1%), rash (1.5%) and white blood cells decreased (1.5%).

Table 5 summarizes the adverse reactions in AK105-202.

Table 5 Adverse Reactions (≥ 10%) in Patients with Recurrent Metastatic Non-Keratinizing NPC Who Received Penpulimab-kcqx in Study AK105-202

Adverse Reaction | Penpulimab-kcqx N = 130
Adverse Reaction | All Grades^1; (%) | Grade 3 or 4^1; (%)
Endocrine disorders
Hypothyroidism^2 | 39 | 0
Musculoskeletal and connective tissue disorders
Musculoskeletal pain^3 | 25 | 0.8
Investigations
Weight decreased | 19 | 1.5
General disorders and administration site conditions
Pyrexia | 15 | 0
Infections and infestations
Upper respiratory tract infection | 13 | 0.8
Respiratory, thoracic and mediastinal disorders
Cough^4 | 11 | 0
Skin and subcutaneous tissue disorders
Rash^5 | 11 | 2.3

^1Graded per NCI CTCAE v5.0

^2Includes blood thyroid stimulating hormone increased

^3Includes arthralgia, back pain, bone pain, musculoskeletal chest pain, neck pain, non-cardiac chest pain, pain in extremity

^4Includes productive cough
^5Includes dermatitis acneiform, eczema, pemphigoid

Table 6 summarizes the laboratory abnormalities in AK105-202.

Table 6 Select Laboratory Abnormalities (≥20%) Worsening from Baseline in Patients with Recurrent Metastatic Non-Keratinizing NPC Who Received Penpulimab-kcqx in Study AK105-202

Laboratory Abnormality | Penpulimab-kcqx
Laboratory Abnormality | All Grades^1; (%)^2 | Grades 3 or 4; (%)
Chemistry
Creatinine increased | 81 | 0
Phosphate decreased | 47 | 8
Sodium decreased | 46 | 6
Albumin decreased | 45 | 0
Triglycerides increased | 38 | 3.1
Alkaline phosphatase increased | 35 | 5
Aspartate aminotransferase increased | 33 | 3.9
GGT increased | 34 | 8
Glucose increased | 34 | 0
Magnesium decreased | 28 | 0.8
Activated partial thromboplastin time prolonged | 22 | 0
Alanine aminotransferase increased | 20 | 3.9
Hematology
Lymphocytes decreased | 43 | 16
Hemoglobin decreased | 36 | 4.7

^1 Toxicity graded according to NCI CTCAE v5.0.
^2 Each test incidence is based on the number of patients who had both baseline and at least one on-study laboratory measurement available: penpulimab-kcqx (range of the patient number: 128 to130).

8 USE IN SPECIFIC POPULATIONS

8.1 Pregnancy

Risk Summary

Based on its mechanism of action, penpulimab-kcqx can cause fetal harm when administered to a pregnant woman [see Clinical Pharmacology (12.1)]. There are no available data on the use of penpulimab-kcqx in pregnant women. Animal studies have demonstrated that inhibition of the PD-1/PD-L1 pathway can lead to increased risk of immune-mediated rejection of the developing fetus resulting in fetal death (see Data). Human immunoglobulin G (IgG) is known to cross the placental barrier; therefore, penpulimab-kcqx has the potential to be transmitted from the mother to the developing fetus. Advise women of the potential risk to a fetus.

In the U.S. general population, the estimated background risk of major birth defects and miscarriage in clinically recognized pregnancies is 2% to 4% and 15% to 20%, respectively.

Data

Animal Data

Animal reproduction studies have not been conducted with penpulimab-kcqx to evaluate its effect on reproduction and fetal development. A central function of the PD-1/PD-L1 pathway is to preserve pregnancy by maintaining maternal immune tolerance to the fetus. In murine models of pregnancy, blockade of PD-L1 signaling has been shown to disrupt tolerance to the fetus and to result in an increase in fetal loss; therefore, potential risks of administering penpulimab-kcqx during pregnancy include increased rates of abortion or stillbirth. As reported in the literature, there were no malformations related to the blockade of PD-1/PD-L1 signaling in the offspring of these animals; however, immune-mediated disorders occurred in PD-1 and PD-L1 knockout mice. Based on its mechanism of action, fetal exposure to penpulimab-kcqx may increase the risk of developing immune-mediated disorders or of altering the normal immune response.

8.2 Lactation

Risk Summary

There is no information regarding the presence of penpulimab-kcqx in human milk or its effects on the breastfed child, or on milk production. Maternal IgG is known to be present in human milk. The effects of local gastrointestinal exposure and limited systemic exposure in the breastfed child to penpulimab-kcqx are unknown. Because of the potential for serious adverse reactions in a breastfed child, advise lactating women not to breastfeed during treatment and for 4 months after the last dose of penpulimab-kcqx.

8.3 Females and Males of Reproductive Potential

Penpulimab-kcqx can cause fetal harm when administered to a pregnant woman [see Use in Specific Populations (8.1)].

Pregnancy Testing

Verify pregnancy status in females of reproductive potential prior to initiating penpulimab-kcqx [see Use in Specific Populations (8.1)].

Contraception

Females

Advise females of reproductive potential to use effective contraception during treatment with penpulimab-kcqx and for 4 months after the last dose.

8.4 Pediatric Use

The safety and effectiveness of penpulimab-kcqx have not been established in pediatric patients [see Indications and Usage (1)].

8.5 Geriatric Use

Penpulimab-kcqx in Combination with Either Cisplatin or Carboplatin and Gemcitabine

Of the 146 patients with NPC who received penpulimab-kcqx in combination with either cisplatin or carboplatin and gemcitabine, 15 (10%) were 65 years or older and 1 (0.7%) was 75 years or older. Clinical studies did not include a sufficient number of patients aged 65 years or older to determine differences in safety or effectiveness compared to younger patients [see Adverse Reactions (6)].

Penpulimab-kcqx as a Single-Agent

Of the 372 patients with NPC who received penpulimab-kcqx as a single agent, 69 (19%) were 65 years or older and 7% were 75 years and older. No overall differences in safety or effectiveness were observed between patients age <65 and those ≥ 65 years [see Adverse Reactions (6)].

11 DESCRIPTION

Penpulimab-kcqx is a programmed death receptor-1 (PD 1)-blocking antibody. Penpulimab-kcqx is a humanized monoclonal IgG1 antibody with an approximate molecular weight of 150 kDa. Penpulimab-kcqx is produced in Chinese hamster ovary (CHO) cells.

Penpulimab-kcqx injection is a sterile, preservative-free, clear to slightly opalescent, colorless to yellowish solution for intravenous infusion after dilution. Each vial contains 100 mg of penpulimab-kcqx in 10 mL solution. Each mL of solution contains: penpulimab-kcqx 10 mg, acetic acid (0.09 mg), polysorbate 80 (0.2 mg), sodium acetate (2.52 mg), sorbitol (45 mg), and Water for Injection, USP. The pH of the solution is 5.8.

12 CLINICAL PHARMACOLOGY

12.1 Mechanism of Action

Binding of the PD-1 ligands, PD-L1 and PD-L2, to the PD-1 receptor found on T cells, inhibits T-cell proliferation and cytokine production. Upregulation of PD-1 ligands occurs in some tumors and signaling through this pathway can contribute to inhibition of active T-cell immune surveillance of tumors. Penpulimab-kcqx injection is a humanized IgG1 monoclonal antibody that binds to PD-1 and blocks its interaction with PD-L1 and PD-L2, releasing PD-1 pathway-mediated inhibition of the immune response, including the anti-tumor immune response. In murine tumor models, blocking PD-1 activity resulted in decreased tumor growth.

12.2 Pharmacodynamics

Penpulimab-kcqx exposure-response relationships and the time course of pharmacodynamic response are not fully characterized.

12.3 Pharmacokinetics

Penpulimab-kcqx exposure increased dose proportionally over the dose range of 1 to 10 mg/kg (0.35 to 3.5 times the approved recommended dosage in a 70 kg patient) after the first dose. The mean accumulation ratio was 1.5 for maximum concentration (Cmax) and 2.1 for area under the concentration curve (AUC) following multiple doses of 200 mg every 3 weeks. Steady-state concentrations of penpulimab-kcqx were reached by Week 15, with mean (CV%) steady-state trough and peak concentrations of 30 μg/mL (38%) and 88 μg/mL (21%), respectively.

Distribution

The mean (CV%) volume of distribution was 10 L (44%).

Elimination

The mean (CV%) clearance was 0.2 L/day (33%) and the mean (CV%) terminal half-life was 32 days (44%).

Metabolism

Penpulimab-kcqx is expected to be metabolized into small peptides by catabolic pathways.

Specific Populations

No clinically significant differences in the pharmacokinetics of penpulimab-kcqx were observed based on body weight (32 to 113 kg), age (18 to 91 years), sex, race (White and Asian), serum albumin (22 to 54.5 g/L), baseline LDH (111 to 4,450 IU/L), baseline C-reactive protein (0 to 328 mg/L), baseline ECOG score (0 and 1), immunogenicity status, tumor type (NPC and other tumors), co-administration (with chemotherapy), mild or moderate renal impairment (creatinine clearance [CLcr] ≥ 30 mL/min), mild (total bilirubin ≤ ULN and AST > ULN or total bilirubin > 1 to 1.5 times ULN and any AST) or moderate hepatic impairment (total bilirubin > 1.5 to 3 times ULN and any AST).

The effect of severe hepatic (total bilirubin > 3 times ULN and any AST) or renal impairment (CLcr < 30 mL/min) on the pharmacokinetics of penpulimab-kcqx is unknown.

12.6 Immunogenicity

The observed incidence of anti-drug antibodies is highly dependent on the sensitivity and specificity of the assay. Differences in assay methods preclude meaningful comparisons of the incidence of anti-drug antibodies in the studies described below with the incidence of anti-drug antibodies in other studies, including those of penpulimab-kcqx or of other penpulimab products.

Of the 349 evaluable patients who received penpulimab-kcqx 1, 3, 10 mg/kg every two weeks or 200 mg every two weeks or every three weeks as a single agent, 30% (105/349) of patients tested positive for anti-drug antibodies (ADA) at one or more post-baseline timepoints. Of those who tested positive for ADA, 17% (18/105) had neutralizing antibodies against penpulimab-kcqx. Of the 371 evaluable patients who received penpulimab-kcqx 200 mg every 3 weeks in combination with chemotherapy, 24% (88/371) of patients tested positive for ADA at one or more post-baseline timepoints. Of those who tested positive for ADA, 44% (39/88) had neutralizing antibodies against penpulimab-kcqx. There are insufficient data to assess whether the observed anti-penpulimab-kcqx antibodies affect the safety or effectiveness of penpulimab-kcqx.

13 NONCLINICAL TOXICOLOGY

13.1 Carcinogenesis, Mutagenesis, Impairment of Fertility

No studies have been performed to assess the potential of penpulimab-kcqx for carcinogenicity or genotoxicity.
Fertility studies have not been conducted with penpulimab-kcqx. In 6-week and 3-month repeat dose toxicology studies in monkeys, there were no notable effects in the male and female reproductive organs; however, most animals in these studies were not sexually mature.

13.2 Animal Toxicology and/or Pharmacology

In animal models, inhibition of PD-1/PD-L1 signaling increased the severity of some infections and enhanced inflammatory responses. Mycobacterium tuberculosis-infected PD-1 knockout mice exhibit markedly decreased survival compared with wild-type controls, which correlated with increased bacterial proliferation and inflammatory responses in these animals. PD-1 blockade using a primate anti-PD-1 antibody was also shown to exacerbate M. tuberculosis infection in rhesus macaques. PD-1 and PD-L1 knockout mice and mice receiving PD-L1 blocking antibody have also shown decreased survival following infection with lymphocytic choriomeningitis virus.

14 CLINICAL STUDIES

14.1 First-line Treatment of Recurrent or Metastatic Nasopharyngeal Carcinoma

The efficacy of penpulimab-kcqx in combination with either cisplatin or carboplatin and gemcitabine was evaluated in Study AK105-304 (NCT04974398), a randomized, double-blind, multi-center trial. The trial included a total of 291 patients with recurrent or metastatic nasopharyngeal carcinoma (NPC). Eligible patients were required to have recurrent NPC with local-regional recurrence and/or distant metastasis occurring ≥ 6 months after completion of curative intent treatment or to have primary metastatic NPC not suitable for local therapy at the time of diagnosis. Patients with autoimmune disease, other than stable hypothyroidism or Type I diabetes, and patients who required systemic immunosuppression were ineligible.

Patients were randomized (1:1) to receive either:

- Penpulimab-kcqx in combination with either cisplatin or carboplatin and gemcitabine, every 3 weeks, for up to 6 cycles, followed by single-agent penpulimab-kcqx every 3 weeks until disease progression or unacceptable toxicity or a maximum of 24 months.
- Placebo in combination with either cisplatin or carboplatin and gemcitabine, every 3 weeks for up to 6 cycles, followed by single-agent placebo every 3 weeks until disease progression or unacceptable toxicity or a maximum of 24 months.

All study medications were administered intravenously.

Randomization was stratified by stage of disease (primary metastatic vs. recurrent), Eastern Cooperative Oncology Group (ECOG) Performance Status (PS) (0 vs. 1), and liver metastasis (present vs. absent).

Patients randomized to placebo were eligible to receive open-label single-agent penpulimab-kcqx (200 mg every 3 weeks) after radiographic disease progression confirmed by blinded independent central review (BICR).

Tumor assessments were performed every 6 weeks for the first 12 months and every 9 weeks thereafter.

The major efficacy outcome measure was BICR-assessed progression-free survival (PFS) according to RECIST v1.1. The key secondary efficacy outcome measure was overall survival (OS).

The study population characteristics were: median age of 51 years (range: 23 to 75), 82% male, 98% Asian, 2.1% White; 1.4% Hispanic or Latino; and 36% ECOG PS of 0. At study entry, 80% of patients had metastatic disease. Histological subtypes of NPC included 96% non-keratinizing, 0.7% keratinizing squamous cell carcinoma, and 3.4% did not have the subtype identified. In total, 98% received cisplatin and 2.4% received carboplatin.

Efficacy results of the analysis of PFS are summarized in Table 7 and Figure 1 below. The trial demonstrated statistically significant improvements in BICR-assessed PFS for patients randomized to penpulimab-kcqx in combination with either cisplatin or carboplatin and gemcitabine compared to placebo with either cisplatin or carboplatin and gemcitabine. OS results were not mature with 70% of pre-specified OS events observed in the overall population.

Table 7 Efficacy Results in AK105-304

Endpoint | Penpulimab-kcqx; cisplatin or carboplatin; and gemcitabine; N=144 | Placebo; cisplatin or carboplatin; and gemcitabine; N=147
BICR-assessed
Progression-free Survival
Number of Events n (%) | 80 (56) | 109 (74)
Median, months (95% CI) | 9.6 (7.1, 12.5) | 7.0 (6.9, 7.3)
Hazard Ratio (95% CI)† | 0.45 (0.33, 0.62)
p-value‡ | <0.0001

†Based on a stratified Cox proportional hazard model.

‡Two-sided p-value, based on the stratified log-rank test, as compared with an alpha boundary of 0.030.

Figure 1 Kaplan-Meier Curves of PFS for AK105-304

14.2 Recurrent Metastatic Non-Keratinizing Nasopharyngeal Carcinoma

The efficacy of single-agent penpulimab-kcqx was evaluated in Study AK105-202 (NCT03866967), an open-label, multicenter, single-arm trial conducted in a single country. The trial included a total of 125 patients with unresectable or metastatic non-keratinizing nasopharyngeal carcinoma (NPC) and who had disease progression after platinum-based chemotherapy and at least one other line of therapy. Patients with a history of autoimmune disease or a medical condition that required immunosuppression were ineligible.

Patients received single-agent penpulimab-kcqx 200 mg intravenously every 2 weeks until disease progression or unacceptable toxicity or a maximum of 24 months. Tumor assessments were performed every 8 weeks in the first year and every 12 weeks thereafter. The major efficacy outcome measures were objective response rate (ORR) and duration of response (DOR) according to RECIST v1.1 as assessed by an Independent Radiology Review Committee (IRRC).

The median age was 50 years (range: 21 to 66 years); 76% were male; 100% were Asian; none were Hispanic or Latino; and Eastern Cooperative Oncology Group (ECOG) performance score (PS) was 0 (31%) or 1 (69%). In total, 10% of patients had tumors with PD-L1 TPS <1%, 50% of patients had tumors with PD-L1 TPS 1-49%, 37% of patients had tumors with PD-L1 TPS ≥50%, and 2.4% of patients had tumors with missing PD-L1 expression levels. Sixty-three percent of patients had received 2 prior lines of chemotherapy, and 37% of patients had received 3 or more prior lines of chemotherapy. Ninety-two percent of patients had received prior radiotherapy.

Efficacy results are summarized in Table 8.

Table 8 Efficacy Results in Study AK105-202

Efficacy Parameter | Penpulimab-kcqx; (N=125)
Objective Response Rate,% (95% CI) | 28 (20, 37)
Complete response rate, % | 0.8
Partial response rate, % | 27
Duration of Response (DOR) | N=35
Mediana, months (95% CI) | NR (9.2, NE)
Patients with DOR ≥ 12 months (%)b | 46

aEstimate using Kaplan-Meier method.

bBased on the observed DOR data.

NR = not reached; NE = not estimable

16 HOW SUPPLIED/STORAGE AND HANDLING

How Supplied

Penpulimab-kcqx injection is a sterile, preservative-free, clear to slightly opalescent, colorless to yellowish solution supplied as:

- Carton containing one 100 mg/10 mL (10 mg/mL) single-dose vial NDC 83654-105-01

Storage and Handling

- Store refrigerated at 2°C to 8°C (36°F to 46°F) in the original carton to protect from light.
- Do not shake. Do not freeze.

17 PATIENT COUNSELING INFORMATION

Advise the patient to read the FDA-approved patient labeling (Medication Guide).

Immune-Mediated Adverse Reactions

Inform patients of the risk of immune-mediated adverse reactions that may be severe or fatal, may occur after discontinuation of treatment, and may require corticosteroid treatment and interruption or discontinuation of penpulimab-kcqx [see Warnings and Precautions (5.1)]. These reactions may include:

- Pneumonitis: Advise patients to contact their healthcare provider immediately for new or worsening cough, chest pain, or shortness of breath [see Warnings and Precautions (5.1)].
- Colitis: Advise patients to contact their healthcare provider immediately for diarrhea or severe abdominal pain [see Warnings and Precautions (5.1)].
- Hepatitis: Advise patients to contact their healthcare provider immediately for jaundice, severe nausea or vomiting, or easy bruising or bleeding [see Warnings and Precautions (5.1) ].
- Endocrinopathies: Advise patients to contact their healthcare provider immediately for signs or symptoms of adrenal insufficiency, hypophysitis, hypothyroidism, hyperthyroidism, or Type 1 diabetes mellitus [see Warnings and Precautions (5.1) ].
- Nephritis: Advise patients to contact their healthcare provider immediately for signs or symptoms of nephritis including decreased urine output, blood in urine, swelling in ankles, loss of appetite, and any other symptoms of renal dysfunction [see Warnings and Precautions (5.1)].
- Severe skin reactions: Advise patients to contact their healthcare provider immediately for any signs or symptoms of severe skin reactions, Stevens-Johnson Syndrome or Toxic Epidermal Necrolysis, including rash or any other severe skin discomfort [see Warnings and Precautions (5.1) ].
- Other immune-mediated adverse reactions:

o Advise patients that immune-mediated adverse reactions can occur and may involve any organ system, and to contact their healthcare provider immediately for any new or worsening signs or symptoms [see Warnings and Precautions (5.1) ].

o Advise patients of the risk of solid organ transplant rejection and other transplant (including corneal graft) rejection. Advise patients to contact their healthcare provider immediately for signs or symptoms of organ transplant rejection and other transplant (including corneal graft) rejection [see Warnings and Precautions (5.1)].

Infusion-Related Reactions

- Advise patients to contact their healthcare provider immediately for signs or symptoms of infusion-related reactions [see Warnings and Precautions (5.2)].

Complications of Allogeneic HSCT

- Advise patients of the risk of post-allogeneic hematopoietic stem cell transplantation complications [see Warnings and Precautions (5.3)].

Embryo-Fetal Toxicity:

- Advise females of reproductive potential that penpulimab-kcqx can cause harm to a fetus and to inform their healthcare provider of a known or suspected pregnancy [see Warnings and Precautions (5.4) and Use in Specific Populations (8.1 , 8.3)].
- Advise females of reproductive potential to use effective contraception during treatment and for 4 months after the last dose of penpulimab-kcqx [see Use in Specific Populations (8.3)].

Lactation:

- Advise female patients not to breastfeed while taking penpulimab-kcqx and for 4 months after the last dose [see Warnings and Precautions (5.4) and Use in Specific Populations (8.2) ].

Manufactured by:

Akeso Biopharma Co., Ltd.

6 Shennong Road, Torch Development Zone, Zhongshan, Guangdong 528437, China

U.S. license number xxxx

MEDICATION GUIDE

PENPULIMAB-KCQX (pen pul i mab kcqx)

injection

What is the most important information I should know about penpulimab-kcqx?

Penpulimab-kcqx is a medicine that may treat non-keratinizing nasopharyngeal cancer by working with your immune system. Penpulimab-kcqx can cause your immune system to attack normal organs and tissues in any area of your body and can affect the way they work. These problems can sometimes become severe or life-threatening and can lead to death. You can have more than one of these problems at the same time. These problems may happen anytime during treatment or even after your treatment has ended.

Call or see your healthcare provider right away if you develop any new or worsening signs or symptoms, including:

Lung problems

- cough

- shortness of breath

- chest pain

Intestinal problems

- diarrhea (loose stools) or more frequent bowel movements than usual
- stools that are black, tarry, sticky, or have blood or mucus
- severe stomach-area (abdomen) pain or tenderness

Liver problems

- yellowing of your skin or the whites of your eyes

- dark urine (tea colored)

- severe nausea or vomiting

- bleeding or bruising more easily than normal

- pain on the right side of your stomach-area (abdomen)

Hormone gland problems

- headaches that will not go away or unusual headaches

- urinating more often than usual

- eye sensitivity to light

- hair loss

- eye problems

- feeling cold

- rapid heartbeat

- constipation

- increased sweating

- your voice gets deeper

- extreme tiredness

- dizziness or fainting

- weight gain or weight loss

- changes in mood or behavior, such as decreased sex drive, irritability, or forgetfulness

- feeling more hungry or thirsty than usual

Kidney problems

- decrease in your amount of urine

- swelling of your ankles

- blood in your urine

- loss of appetite

Skin problems

- rash

- painful sores or ulcers in your mouth or nose, throat, or genital area

- itching

- fever or flu-like symptoms

- skin blistering or peeling

- swollen lymph nodes

Problems can also happen in other organs and tissues. These are not all of the signs and symptoms of immune system problems that can happen with penpulimab-kcqx. Call or see your healthcare provider right away for any new or worsening signs or symptoms, which may include:

- chest pain, irregular heartbeat, shortness of breath, swelling of ankles
- confusion, sleepiness, memory problems, changes in mood or behavior, stiff neck, balance problems, tingling or numbness of the arms or legs
- double vision, blurry vision, sensitivity to light, eye pain, changes in eyesight
- persistent or severe muscle pain or weakness, muscle cramps
- low red blood cells, bruising

Infusion reactions that can sometimes be severe or life-threatening. Signs and symptoms of infusion reactions may include:

- chills or shaking

- dizziness

- itching or rash

- feeling like passing out

- flushing

- fever

- shortness of breath or wheezing

- back pain

Rejection of a transplanted organ or tissue. Your healthcare provider should tell you what signs and symptoms you should report and monitor you depending on the type of organ or tissue transplant that you have had.

Complications, including graft-versus-host-disease (GVHD), in people who have received a bone marrow (stem cell) transplant that uses donor stem cells (allogeneic). These complications can be serious and can lead to death. These complications may happen if you underwent transplantation either before or after being treated with penpulimab-kcqx. Your healthcare provider will monitor you for these complications.

Getting medical treatment right away may help keep these problems from becoming more serious. Your healthcare provider will check for these problems during treatment with penpulimab-kcqx. Your healthcare provider may treat you with corticosteroid or hormone replacement medicines. Your healthcare provider may also need to delay or completely stop treatment with penpulimab-kcqx if you have severe side effects.

What is penpulimab-kcqx?

Penpulimab-kcqx is a prescription medicine used to treat adults with a kind of cancer called non-keratinizing nasopharyngeal carcinoma (NPC).

- Penpulimab-kcqx may be used in combination with either the chemotherapy medicines cisplatin or carboplatin and gemcitabine, as your first treatment when your non-keratinizing NPC has returned (recurrent) or has spread to other parts of your body (metastatic).
- Penpulimab-kcqx may be used alone to treat your non-keratinizing NPC when it:

- has spread (metastatic), and
- you received chemotherapy that contains platinum and at least 1 other type of treatment, and it did not work or is no longer working.

It is not known if penpulimab-kcqx is safe and effective in children.

Before receiving penpulimab-kcqx, tell your healthcare provider about all of your medical conditions, including if you:

- have immune system problems such as Crohn’s disease, ulcerative colitis, or lupus
- have received an organ transplant, including corneal transplant
- have received or plan to receive a stem cell transplant that uses donor stem cells (allogeneic)
- have received radiation treatment to your chest area
- have a condition that affects your nervous system, such as myasthenia gravis or Guillain-Barré syndrome
- are pregnant or plan to become pregnant. Penpulimab-kcqx can harm your unborn baby.

Females who are able to become pregnant:

- Your healthcare provider will give you a pregnancy test before you start treatment with penpulimab-kcqx.

- You should use an effective method of birth control during your treatment and for 4 months after your last dose of penpulimab-kcqx. Talk to your healthcare provider about birth control methods that you can use during this time.
- Tell your healthcare provider right away if you become pregnant or think you may be pregnant during treatment with penpulimab-kcqx.

- are breastfeeding or plan to breastfeed. It is not known if penpulimab-kcqx passes into your breast milk. Do not breastfeed during treatment with penpulimab-kcqx and for 4 months after your last dose of penpulimab-kcqx.

Tell your healthcare provider about all the medicines you take, including prescription and over-the-counter medicines, vitamins, and herbal supplements.

How will I receive penpulimab-kcqx?

- Your healthcare provider will give you penpulimab-kcqx into your vein through an intravenous (IV) line over 60 minutes.
- Penpulimab-kcqx is usually given every 2 or 3 weeks.
- Your healthcare provider will decide how many treatments you need.
- Your healthcare provider will test your blood to check you for certain side effects.
- If you miss any appointments, call your healthcare provider as soon as possible to reschedule your appointment.

What are the possible side effects of penpulimab-kcqx?

Penpulimab-kcqx can cause serious side effects. See “What is the most important information I should know about penpulimab-kcqx?”

The most common side effects of penpulimab-kcqx when used in combination with either cisplatin or carboplatin and gemcitabine include:

- nausea

- decreased appetite

- feeling tired

- vomiting

- decreased weight

- rash

- low thyroid hormone levels

- cough

- fever

- constipation

- COVID-19 infection

The most common side effects of penpulimab-kcqx when used alone include low red blood cell count (anemia) and low thyroid hormone levels.

These are not all the possible side effects of penpulimab-kcqx.

Call your doctor for medical advice about side effects. You may report side effects to FDA at 1-800-FDA-1088.

General information about the safe and effective use of penpulimab-kcqx.

Medicines are sometimes prescribed for purposes other than those listed in a Medication Guide. You can ask your pharmacist or healthcare provider for information about penpulimab-kcqx that is written for healthcare professionals.

What are the ingredients in penpulimab-kcqx?

Active ingredient: penpulimab-kcqx

Inactive ingredients: acetic acid, polysorbate 80, sodium acetate, sorbitol, and Water for Injection.

Manufactured by: Akeso Biopharma Co., Ltd., 6 Shennong Road, Torch Development Zone, Zhongshan, Guangdong 528437, China

U.S. License No. xxxx

For more information, call 833-662-5376 or go to https://www.akesobio.com/en/.

This Medication Guide has been approved by the U.S. Food and Drug Administration. Issued: April/2025